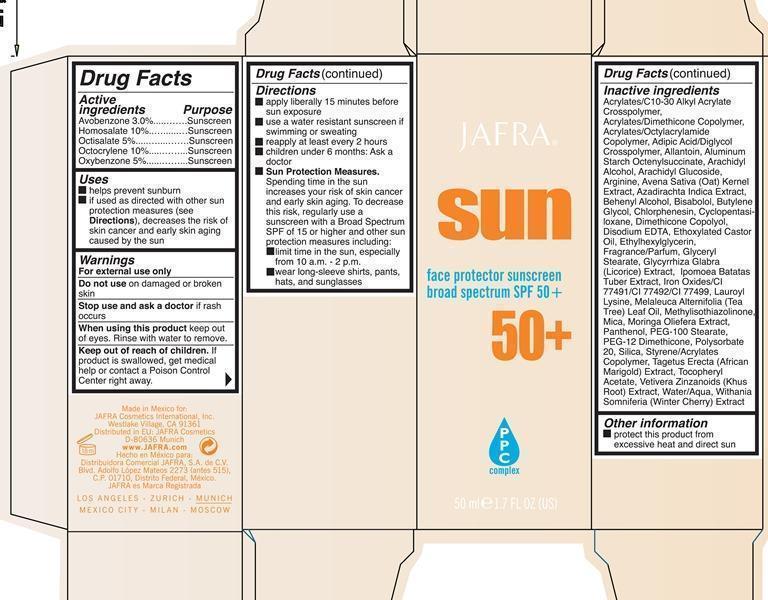 DRUG LABEL: Sun Face Protector Sunscreen Broad Spectrum SPF 50

NDC: 68828-188 | Form: LOTION
Manufacturer: Jafra Cosmetics International Inc
Category: otc | Type: HUMAN OTC DRUG LABEL
Date: 20200622

ACTIVE INGREDIENTS: AVOBENZONE 3 g/100 mL; HOMOSALATE 10 g/100 mL; OCTISALATE 5 g/100 mL; OCTOCRYLENE 10 g/100 mL; OXYBENZONE 10 g/100 mL
INACTIVE INGREDIENTS: CARBOMER COPOLYMER TYPE A (ALLYL PENTAERYTHRITOL CROSSLINKED); ALLANTOIN; ALUMINUM STARCH OCTENYLSUCCINATE; ARACHIDYL ALCOHOL; ARACHIDYL GLUCOSIDE; ARGININE; OAT; AZADIRACHTA INDICA BARK; DOCOSANOL; LEVOMENOL; BUTYLENE GLYCOL; CHLORPHENESIN; CYCLOMETHICONE 5; EDETATE DISODIUM; ETHYLHEXYLGLYCERIN; GLYCERYL MONOSTEARATE; LICORICE; SWEET POTATO; FERRIC OXIDE RED; FERRIC OXIDE YELLOW; FERROSOFERRIC OXIDE; LAUROYL LYSINE; TEA TREE OIL; METHYLISOTHIAZOLINONE; MICA; MORINGA OLEIFERA BARK; PANTHENOL; PEG-100 STEARATE; PEG-12 DIMETHICONE (300 CST); POLYSORBATE 20; SILICON DIOXIDE; TAGETES ERECTA FLOWER; .ALPHA.-TOCOPHEROL ACETATE; CHRYSOPOGON ZIZANIOIDES ROOT; WATER; WITHANIA SOMNIFERA FLOWER

Sun Face Protector Broad Spectrum 50+

Active ingredients Purpose

Avobenzone 3% Sunscreen

Homosalate 10% Sunscreen

Octisalate 5% Sunscreen

Octocrylene 10% Sunscreen

Oxybenzone 5% Sunscreen

Uses

helps prevent sunburn

if used as directed with other sun protection measures (see Directions), decreases the risk of skin cancer and early skin aging caused by the sun

Keep out of reach of children

Stop use and ask a doctor if rash occurs

Warnings

For external use only

Do not use on damaged or broken skin

When using this product keep out of eyes. Rinse with water to remove

If product is swallowed, get medical help or contact a Poison Control Center right away.

Directions

apply liberally 15 minutes before sun exposure

use a water resistant sunscreen if swimming or sweating

reapply at least every 2 hours

children under 6 months: ask a doctor

Sun Protection Measures

Inactive ingredients

Acrylates/C10-30 Alkyl Acrylate Crosspolymer, Acrylates/Dimethicone Copolymer, Acrylates/Octylacrylamide Copolymer, Adipic Acid/Diglycol Crosspolymer, Allantoin, Alluminium Starch Octenylsuccinate, Arachidyl Alcohol, Arachidyl Glucoside, Arginine, Avena Sativa (Oat) Kernel Extract, Azadirachta Indica Extract, Behenyl Alcohol, Bisabolol, Butylene Glycol, Chlorphenesin, Cyclopentasiloxane, Dimethicone Copolyol, Disodium EDTA, Ethoxylated Castor Oil, Ethylhexyglycerin, Fragrance/Parfum, Glyceryl Stearate, Glycyrrhiza Glabra (Licorice) Extract, Ipomoea Batatas Tuber Extract, Iron Oxides/CI 77491/CI 77492/CI 77499, Lauroyl Lysine, Melaleuca Alternifolia (Tea Tree) Leaf Oil, Methylisothiazolinone, Mica, Moringa Oliefera Extract, Panthenol, PEG-100 Stearate, PEG-12 Dimethicone, Polysorbate 20, Silica, Styrene/Acrylates Copolymer, Tagetus Erecta (African Marigold) Extract, Tocopheryl Acetate, Vetivera Zinzanoids (Khus Root) Extract, Water/Aqua, Withania Somnifera (Winter Cherry) Extract

PACKAGE LABEL

Jafra Sun Face Protector Sunscreen broad spectrum SPF 50+

50 ml 1.7 FL OZ (US)